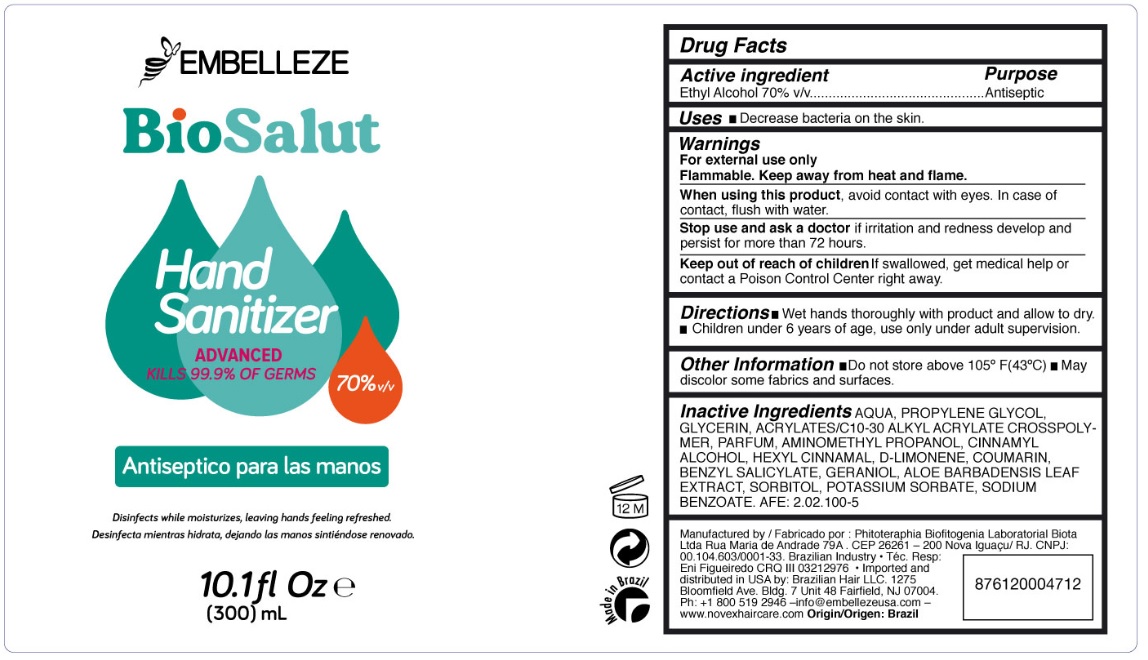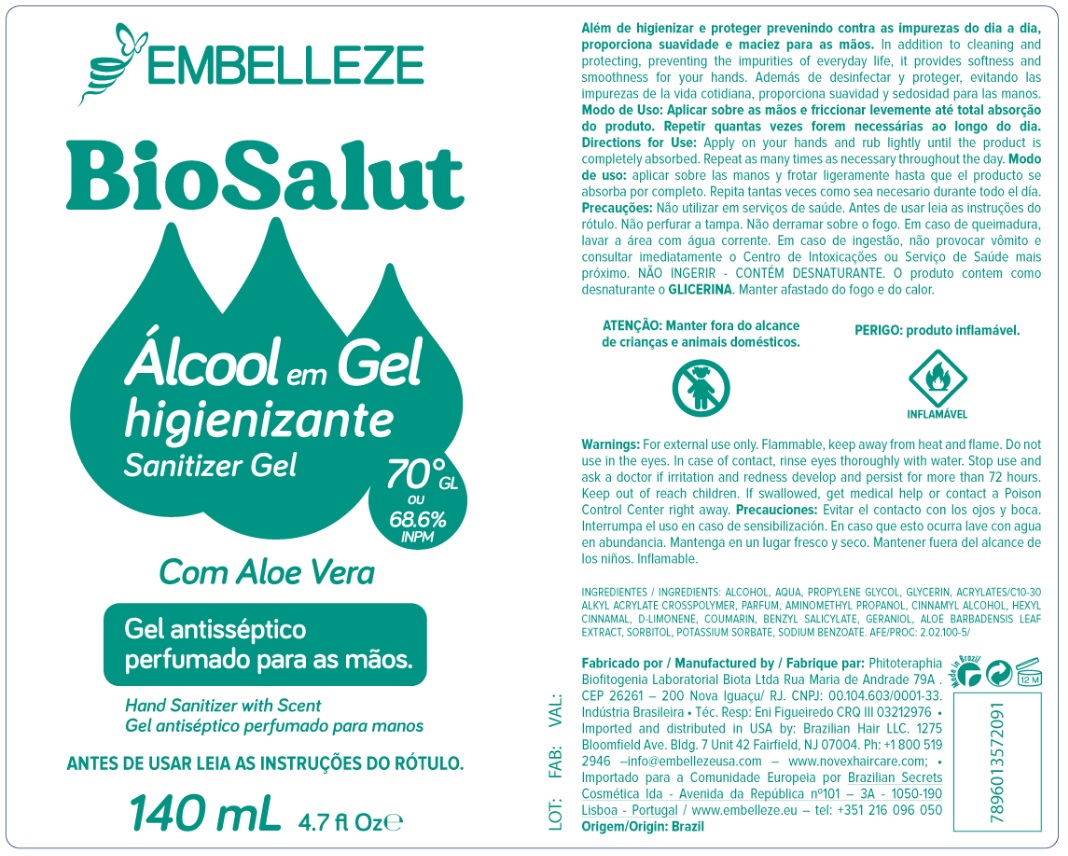 DRUG LABEL: BioSalut Hand Sanitizer Advanced
NDC: 75753-300 | Form: GEL
Manufacturer: Brazilian Hair Llc
Category: otc | Type: HUMAN OTC DRUG LABEL
Date: 20200914

ACTIVE INGREDIENTS: ALCOHOL 70 mL/100 mL
INACTIVE INGREDIENTS: WATER; PROPYLENE GLYCOL; GLYCERIN; CARBOMER INTERPOLYMER TYPE A (ALLYL SUCROSE CROSSLINKED); AMINOMETHYLPROPANOL; CINNAMYL ALCOHOL; .ALPHA.-HEXYLCINNAMALDEHYDE; LIMONENE, (+)-; COUMARIN; BENZYL SALICYLATE; GERANIOL; ALOE VERA LEAF; SORBITOL; POTASSIUM SORBATE; SODIUM BENZOATE

EMBELLEZE BioSalut Hand Sanitizer ADVANCED

Active ingredient

Ethyl Alcohol 70% v/v

Purpose

Antiseptic

INDICATIONS AND USAGE

Uses • Decrease bacteria on the skin.

Warnings

For external use only

Flammable. Keep away from heat and flame.

When using this product, avoid contact with eye. In case of contact, flush with water.

Stop use and ask a doctor if irritation and redness develop and persist for more than 72 hours.

Keep out of reach of children If swallowed, get medical help or contact a Poison Control Centre right away.

DOSAGE AND ADMINISTRATION

Directions• Wet hands thoroughly with product and allow to dry. • Children under 6 years of age, use only under adult supervision.

Other Information • Do not store above 105°F (43°C) • May discolor some fabrics and surfaces.

INACTIVE INGREDIENT

Inactive Ingredients AQUA, PROPYLENE GLYCOL, GLYCERIN, ACRYLATES/C10-30 ALKYL ACRYLATE CROSSPOLYMER, PARFUM, AMINOMETHYL PROPANOL, CINNAMYL ALCOHOL, HEXYL CINNAMAL, D-LIMONENE, COUMARIN, BENZYL SALICYLATE, GERANIOL, ALOE BARBADENSIS LEAF EXTRACT, SORBITOL, POTASSIUM SORBATE, SODIUM BENZOATE. AFE: 2.02.100-5

KILLS 99.9% OF GERMS

Disinfects while moisturizes, leaving hands feeling refreshed.

Manufactured by : Phitoteraphia Biofitogenia Laboratorial Biota

Ltda Rua Maria de Andrade 79A . CEP 26261 - 200 Nova Iguaçu/RJ. CNPJ:

00.104.603/0001-33. Brazilian Industry • Téc. Resp:

Eni Figueiredo CRQ III 03212976 • Imported and distributed in USA by: Brazilian Hair LLC. 1275

Bloomfield Ave. Bldg. 7 Unit 48 Fairfield, NJ 07004.

Ph: +1 800 519 2946 -info@embellezeusa.com - www.novexhaircare.com Origin/Origen: Brazil